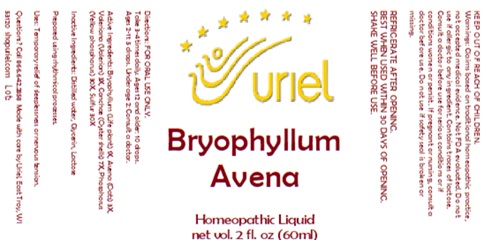 DRUG LABEL: Bryophyllum Avena
NDC: 48951-2137 | Form: LIQUID
Manufacturer: Uriel Pharmacy Inc
Category: homeopathic | Type: HUMAN OTC DRUG LABEL
Date: 20250528

ACTIVE INGREDIENTS: OAT 3 [hp_X]/1 mL; VALERIAN 3 [hp_X]/1 mL; OYSTER SHELL CALCIUM CARBONATE, CRUDE 7 [hp_X]/1 mL; PHOSPHORUS 30 [hp_X]/1 mL; SULFUR 30 [hp_X]/1 mL; KALANCHOE DAIGREMONTIANA LEAF 1 [hp_X]/1 mL
INACTIVE INGREDIENTS: WATER; GLYCERIN; LACTOSE, UNSPECIFIED FORM

Bryophyllum Avena

INDICATIONS AND USAGE

Directions: FOR ORAL USE ONLY.

DOSAGE AND ADMINISTRATION

Take 3-4 times daily. Ages 12 and older: 10 drops.
Ages 2-11: 5 drops. Under age 2: Consult a doctor.

ACTIVE INGREDIENT

Active Ingredients: Bryophyllum (Life plant) 1X, Avena (Oats) 3X, Valeriana (Valerian) 3X, Conchae (Oyster shells) 7X, Phosphorus (Yellow phosphorus) 30X, Sulfur 30X

Inactive Ingredients: Distilled water, Glycerin, Lactose

Prepared using rhythmical processes.

KEEP OUT OF REACH OF CHILDREN.

PURPOSE

Uses: Temporary relief of sleeplessness or nervous tension.

WARNINGS

Warnings: Claims based on traditional homeopathic practice, not accepted medical evidence. Not FDA evaluated. Do not use if allergic to any ingredient. Contains traces of lactose. Consult a doctor before use for serious conditions or if conditions worsen or persist. If pregnant or nursing, consult a doctor before use. Do not use if safety seal is broken or missing.

REFRIGERATE AFTER OPENING.
BEST WHEN USED WITHIN 30 DAYS OF OPENING.

SHAKE WELL BEFORE USE.

Questions? Call 866.642.2858
Made with care by Uriel, East Troy, WI 53120
shopuriel.com